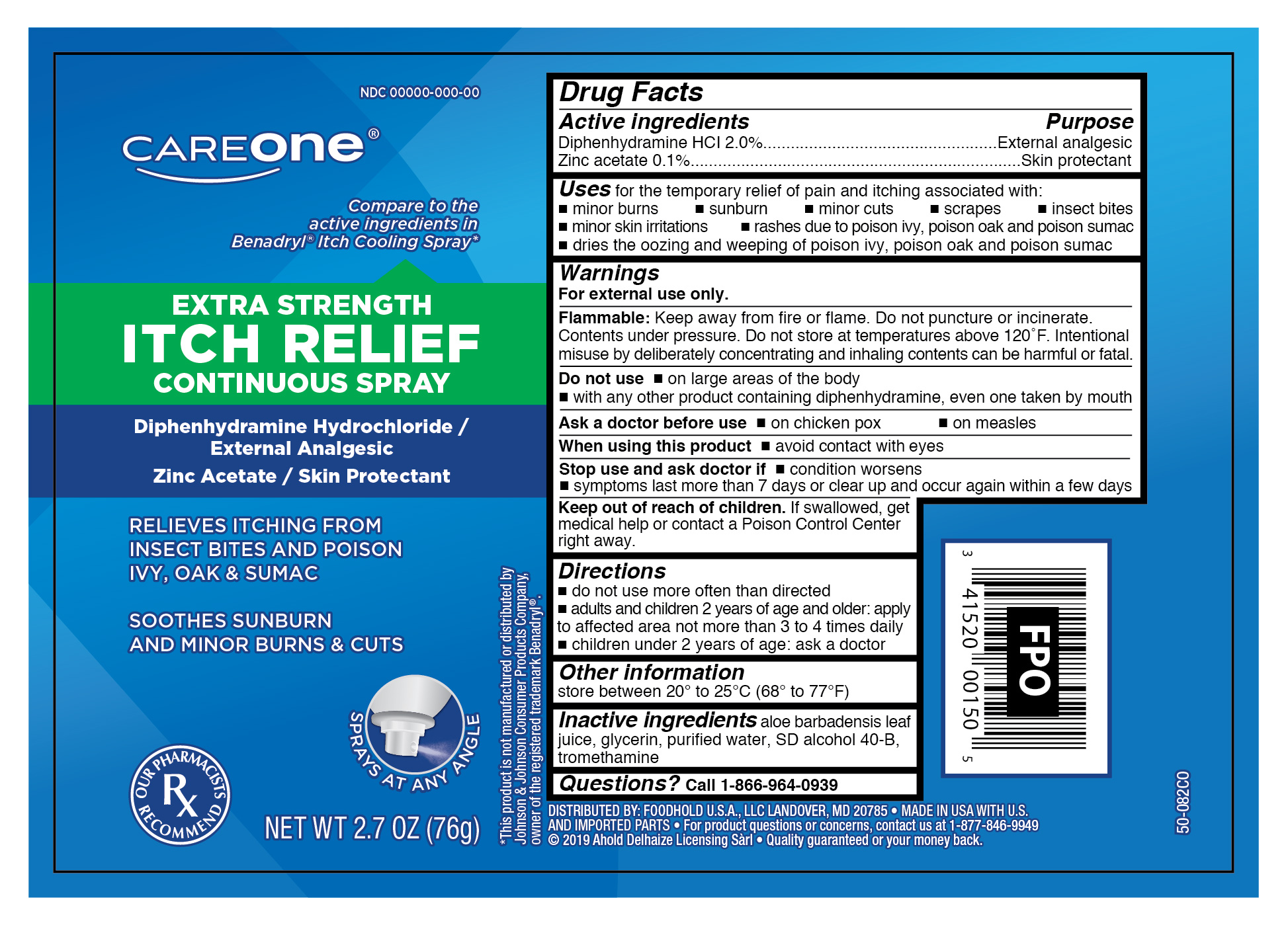 DRUG LABEL: Diphenhydramine HCI and Zinc Acetate
NDC: 41520-090 | Form: AEROSOL, SPRAY
Manufacturer: Foodhold USA
Category: otc | Type: HUMAN OTC DRUG LABEL
Date: 20190130

ACTIVE INGREDIENTS: BROMODIPHENHYDRAMINE HYDROCHLORIDE 1.52 g/76 g; ZINC ACETATE 0.076 g/76 g
INACTIVE INGREDIENTS: GLYCERIN; TROMETHAMINE; ALOE VERA LEAF; WATER; ALCOHOL

CareOne Extra Strength Itch Relief Continuous Spray

Active Ingredients

Diphenhydramine HCI 2.0%

Zinc Acetate 0.1%

Purpose

External Analgesic

Skin Protectant

Uses

for the temporary relief of pain and itching associated with:

- minor burns
- sunburn
- minor cuts
- scrapes
- insect bites
- minor skin irritations
- rashes due to poison ivy, poison oak and poison sumac
- dries the oozing and weeping of poison ivy, poison oak and poison sumac

Warnings

For external use only.

Flammable:

Keep away from fire or flame. Do not puncture or incinerate. Contents under pressure. Do not store at temperatures above 120ºF. Intentional misuse by deliberately concentrating and inhaling contents can be harmful or fatal.

Do not use

- on lare areas of the body
- with any other product containing diphenhydramine, even one taken by mouth

Ask a doctor before use

- on chicken pox
- on measles

When using this product

- avoid contact with eyes

Stop use and ask doctor if

- condition worsens
- symptoms last more than 7 days or clear up and occur again within a few days

Keep out of the reach of children.

If swallowed, get medical help or contact a Poison Control Center right away.

Directions

- do not use more often than directed
- adults and children 2 years of age and older: apply to affected area not more than 3 to 4 times daily
- children under 2 years of age: ask a doctor

Other Information

store between 20º to 25ºC (68º to 77ºF)

Inactive Ingredients

aloe barbadensis leaf juice, glycerin, purified water, SD alcohol 40-B, tromethamine

Questions?

Call 1-866-964-0939

Principal Display Panel

CAREONE

Extra Strength Itch Relief Continuous Spray

Diphenhydramine Hydrochloride/

External Analgesic

Zinc Acetate / Skin Protectant

RELIEFS ITCHING FROM

INSECT BITES AND POISON

IVY, OAK & SUMAC

SOOTHES SUNBURN

AND MINOR BURNS & CUTS

NET WT 2.7 OZ (76g)